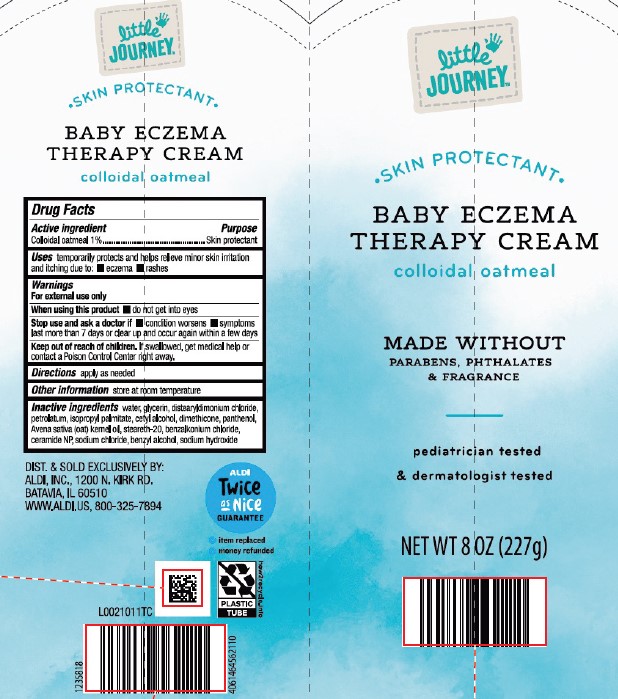 DRUG LABEL: Baby Eczema Therapy
NDC: 64024-601 | Form: CREAM
Manufacturer: Aldi, Inc
Category: otc | Type: HUMAN OTC DRUG LABEL
Date: 20260129

ACTIVE INGREDIENTS: OATMEAL 10 mg/1 g
INACTIVE INGREDIENTS: WATER; GLYCERIN; DISTEARYLDIMONIUM CHLORIDE; PETROLATUM; ISOPROPYL PALMITATE; CETYL ALCOHOL; DIMETHICONE; PANTHENOL; OAT KERNEL OIL; STEARETH-20; BENZALKONIUM CHLORIDE; CERAMIDE NP; SODIUM CHLORIDE; BENZYL ALCOHOL; SODIUM HYDROXIDE

Little Journey 601.001/601AC
Baby Eczema Therapy Cream

Claims

Little Journey™

SKIN PROTECTANT

BABY ECZEMA

THERAPY CREAM

colloidal oatmeal

Active ingredient

Colloidal oatmeal 1%

Purpose

Skin protectant

Uses

temporarily protects and helps relieve minor skin irritation and itching due to:

- eczema
- rashes

Warnings

For external use only

When using this product

- do not get into eyes

Stop use and ask a doctor if

- condition worsens
- symptoms last more than 7 days or clear up and occur again within a few days

Keep out of reach of children.

If swallowed, get medical help or contact a Poison Control Center right away.

Directions

apply as needed.

Other information

store at room temperature.

Inactive ingredients

water, glycerin, distearyldimonium chloride, petrolatum, isopropyl palmitate, cetyl alcohol, dimethicone, panthenol, Avena sativa (oat) kernel oil, steareth-20, benzalkonium chloride, ceramide NP, sodium chloride, benzyl alcohol, sodium hydroxide

Adverse reaction

DIST. & SOLD EXCLUSIVELY BY:

ALDI, Inc., 1200 N. Kirk Rd.

BATAVIA, IL 60510

ALDI TWICE AS NICE GUARANTEE

- item replaced
- money refunded

PLASTIC TUBE

how2recycle.info

Principal display panel

Little Journey™

SKIN PROTECTANT

BABY ECZEMA

THERAPY CREAM

colloidal oatmeal

MADE WITHOUT PARABENS, PHTHALATES & FRAGRANCE

pediatrician tested & dermatologist tested

NET WT 8 OZ (227 g)